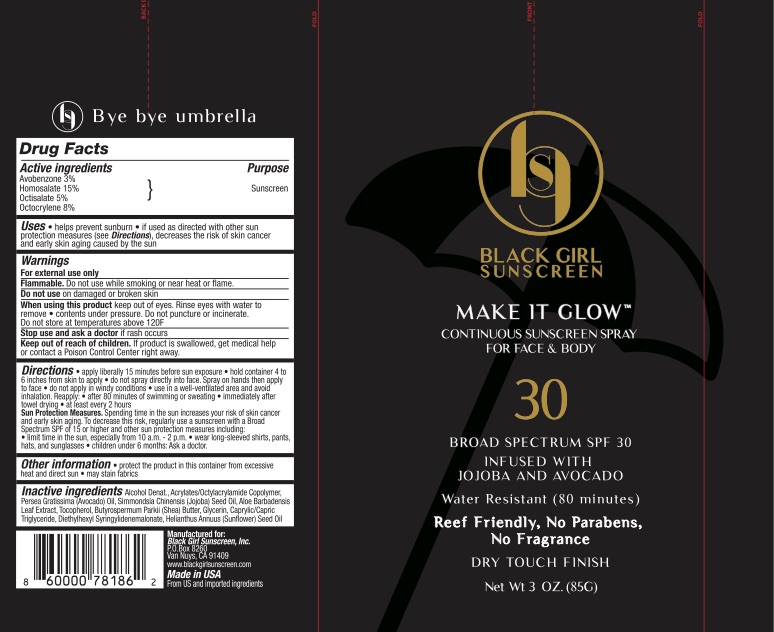 DRUG LABEL: Black Girl Sunscreen SPF 30
NDC: 72839-121 | Form: SPRAY
Manufacturer: Derma Care Research Labs, LLC
Category: otc | Type: HUMAN OTC DRUG LABEL
Date: 20241219

ACTIVE INGREDIENTS: OCTISALATE 5 g/100 g; AVOBENZONE 3 g/100 g; HOMOSALATE 15 g/100 g; OCTOCRYLENE 8 g/100 g
INACTIVE INGREDIENTS: ALOE VERA LEAF; GLYCERIN; ACRYLATE/ISOBUTYL METHACRYLATE/N-TERT-OCTYLACRYLAMIDE COPOLYMER (75000 MW); CAPRYLYL TRISILOXANE; MEDIUM-CHAIN TRIGLYCERIDES; DIETHYLHEXYL SYRINGYLIDENEMALONATE; TOCOPHEROL; ALCOHOL; SUNFLOWER OIL; JOJOBA OIL; AVOCADO OIL; SHEA BUTTER

Active Ingredients

Avobenzone 3%, Homosalate 15%, Octisalate 5%, Octocrylene 8%

Purpose

Sunscreen

Uses

- Helps prevent sunburn.
- If used as directed with other sun protection measures (see Directions), decreases the risk of skin cancer and early skin aging caused by the sun.

Warnings

For external use only. Flammable: do not use while smoking or near heat or flame.

Do not use on damaged or broken skin. When using this product keep out of eyes. Rinse eyes with water to remove. Contents under pressure. Do not puncture or incinerate. Do not store at temperature above 120 degrees F.

Stop use and ask a doctor if rash occurs.

Keep Out of Reach of Children.

If swallowed, get medical help or contact a Poison Control Center right away.

Directions

Apply liberally 15 minutes before sun exposure. Reapply:

- after 80 minutes of swimming or sweating
- immediately after towel drying
- at least every 2 hours

Sun protection measures: spending time n the sun increases your risk of skin cancer and early skin aging. To decrease risk, regularly use a sunscreen with broad spectrum SPF of 15 or higher and other sun protection measure including:

- limit time in the sun, especially from 10 am to 2 pm
- wear long-sleeved shirts, pants, hats, and sunglasses.
- Children under 6 months: ask a doctor.

Hold container 4 to 6 inches from the skin to apply. Do not spray directly into face. Spray on hands then apply to face. Do no apply in windy conditions. Use in a well-ventilated area.

Inactive Ingredients

Alcohol Denat., Acrylates/Octylacrylamide Copolymer, Persea Gratissima (Avocado) Oil, Simmondsia Chinensis (Jojoba) Seed Oil, Aloe Barbadensis Leaf Extract, Tocopherol, Butyrospermum Parkii (Shea) Butter, Glycerin, Caprylic/Capric Triglyceride, Diethylhexyl Syringylidenemalonate, Helianthus Annuus (Sunflower) Seed Oil.